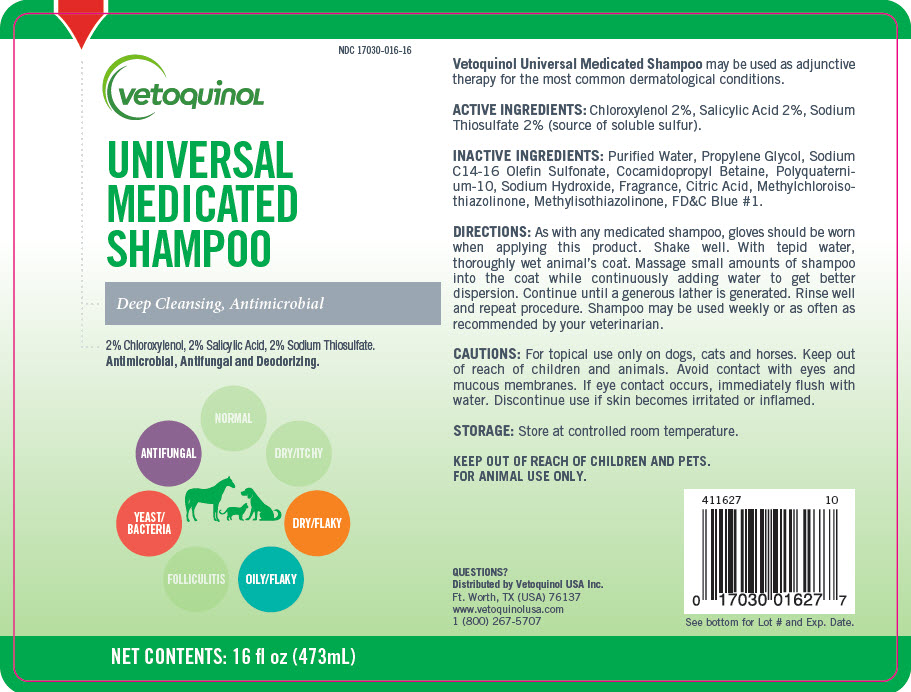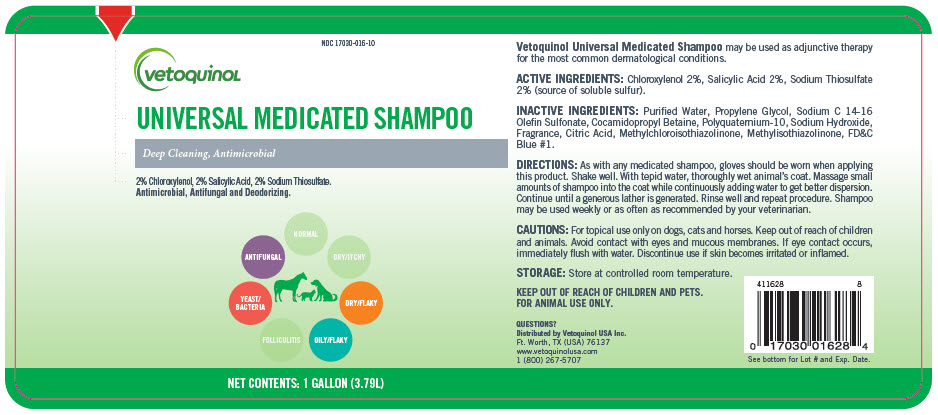 DRUG LABEL: UNIVERSAL MEDICATED
NDC: 17030-016 | Form: SHAMPOO
Manufacturer: Vetoquinol USA, Inc.
Category: animal | Type: OTC ANIMAL DRUG LABEL
Date: 20201214

ACTIVE INGREDIENTS: Chloroxylenol 20 mg/1 mL; Salicylic Acid 20 mg/1 mL; Sodium Thiosulfate 20 mg/1 mL
INACTIVE INGREDIENTS: Water; Propylene Glycol; Sodium C14-16 Olefin Sulfonate; Cocamidopropyl Betaine; Polyquaternium-10 (125 MPA.S at 2%); Sodium Hydroxide; Citric Acid Monohydrate; Methylchloroisothiazolinone; Methylisothiazolinone; FD&C BLUE NO. 1

UNIVERSAL MEDICATED SHAMPOO
Deep Cleansing, Antimicrobial

VETERINARY INDICATIONS

Vetoquinol Universal Medicated Shampoo may be used as adjunctive therapy for the most common dermatological conditions.

ACTIVE INGREDIENTS: Chloroxylenol 2%, Salicylic Acid 2%, Sodium Thiosulfate 2% (source of soluble sulfur).

INACTIVE INGREDIENTS: Purified Water, Propylene Glycol, Sodium C14-16 Olefin Sulfonate, Cocamidopropyl Betaine, Polyquaternium-10, Sodium Hydroxide, Fragrance, Citric Acid, Methylchloroisothiazolinone, Methylisothiazolinone, FD&C Blue #1.

DOSAGE AND ADMINISTRATION

DIRECTIONS: As with any medicated shampoo, gloves should be worn when applying this product. Shake well. With tepid water, thoroughly wet animal's coat. Massage small amounts of shampoo into the coat while continuously adding water to get better dispersion. Continue until a generous lather is generated. Rinse well and repeat procedure. Shampoo may be used weekly or as often as recommended by your veterinarian.

CAUTIONS: For topical use only on dogs, cats and horses. Keep out of reach of children and animals. Avoid contact with eyes and mucous membranes. If eye contact occurs, immediately flush with water. Discontinue use if skin becomes irritated or inflamed.

STORAGE: Store at controlled room temperature.

KEEP OUT OF REACH OF CHILDREN AND PETS.
FOR ANIMAL USE ONLY.

QUESTIONS?

Distributed by Vetoquinol USA Inc.
Ft. Worth, TX (USA) 76137
www.vetoquinolusa.com
1 (800) 267-5707

411627
10

See bottom for Lot # and Exp. Date.

PRINCIPAL DISPLAY PANEL - 473 mL Bottle Label

NDC 17030-016-16

vetoquinoL

UNIVERSAL
MEDICATED
SHAMPOO

Deep Cleansing, Antimicrobial

2% Chloroxylenol, 2% Salicylic Acid, 2% Sodium Thiosulfate.
Antimicrobial, Antifungal and Deodorizing.

ANTIFUNGAL
YEAST/
BACTERIA
OILY/FLAKY
DRY/FLAKY

NET CONTENTS: 16 fl oz (473mL)

PRINCIPAL DISPLAY PANEL - 3.79 L Bottle Label

NDC 17030-016-10

vetoquinoL

UNIVERSAL MEDICATED SHAMPOO

Deep Cleansing, Antimicrobial

2% Chloroxylenol, 2% Salicylic Acid, 2% Sodium Thiosulfate.
Antimicrobial, Antifungal and Deodorizing.

ANTIFUNGAL
YEAST/
BACTERIA
OILY/FLAKY
DRY/FLAKY

NET CONTENTS: 1 GALLON (3.79L)